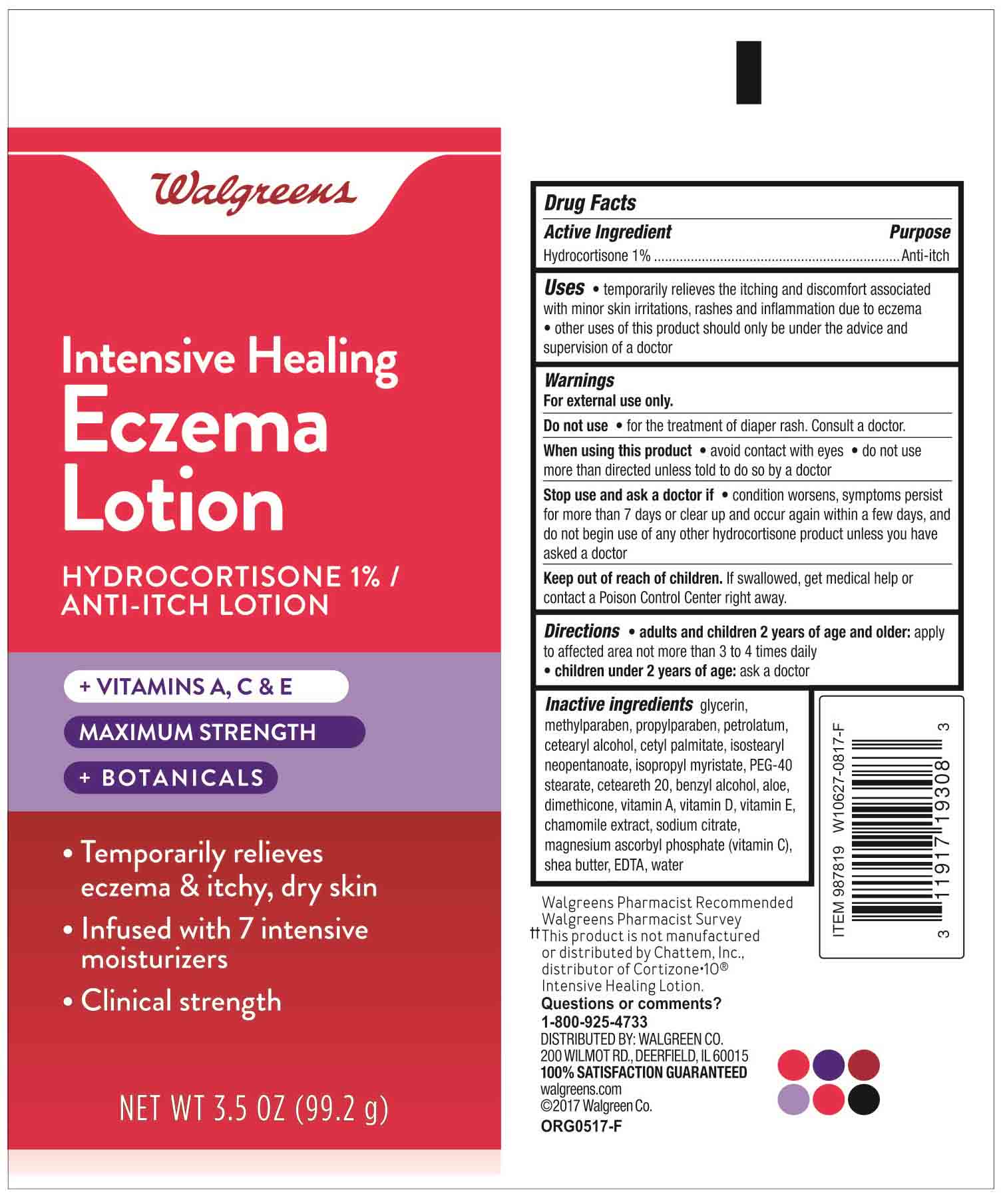 DRUG LABEL: Intensive Healing Eczema
NDC: 0363-0670 | Form: LOTION
Manufacturer: Walgreens
Category: otc | Type: HUMAN OTC DRUG LABEL
Date: 20180204

ACTIVE INGREDIENTS: HYDROCORTISONE 1.02 g/100 g
INACTIVE INGREDIENTS: WATER 64.89 g/100 g; GLYCERIN 15 g/100 g; CETOSTEARYL ALCOHOL 5 g/100 g; CETYL PALMITATE 3 g/100 g; POLYOXYL 20 CETOSTEARYL ETHER 3 g/100 g; PETROLATUM 2 g/100 g; ISOPROPYL MYRISTATE 1.5 g/100 g; ALOE VERA LEAF 1.0 g/100 g; BENZYL ALCOHOL 1.0 g/100 g; ISOSTEARYL NEOPENTANOATE .5 g/100 g; PEG-40 STEARATE .5 g/100 g; EDETATE DISODIUM .5 g/100 g; SHEA BUTTER .5 g/100 g; METHYLPARABEN .2 g/100 g; PROPYLPARABEN .1 g/100 g; CHAMOMILE .1 g/100 g; SODIUM CITRATE .1 g/100 g; VITAMIN A PALMITATE .02 g/100 g; CHOLECALCIFEROL .02 g/100 g; .ALPHA.-TOCOPHEROL ACETATE, D- .02 g/100 g; MAGNESIUM ASCORBYL PHOSPHATE .02 g/100 g; DIMETHICONE .01 g/100 g

Active Ingredient

Hydrocortisone 1%

Purpose

Anti-Itch

Uses

Temporarily relieves the itching and discomfort associated with minor skin irritations, rashes and inflammation due to excema.

Other uses of this product should only be under the advice and supervision of a doctor.

Warnings

For external use only.

Do not use for the treatment of diaper rash. Consult a doctor.

When using this product

avoid contact with the eyes.

do not use more than directed unless told to do so by a doctor.

Stop use and ask a doctor if

condition worsens, symptoms persist for more than 7 days or clear up and occur again within a few days, and do not begin use of any other hydrocortisone product unless you have asked a doctor.

Keep out of reach of children.

If swallowed, get medical help or contact a Poison Control Center right away.

Directions

adults and children 2 years of age or older: apply to affected area not more than 3 to 4 times daily.

children under 2 years of age: ask a doctor.

Inactive Ingredients

glycerin, methylparaben, propylparaben, petrolatum, cetearyl alcohol, cetyl palmitate, isostearyl neopentanoate, isopropyl myristate, PEG-40 stearate, ceteareth 20, benzyl alcohol, aloe, dimethicone, vitamin A, vitamin D, vitamin E, chamomile extract, sodium citrate, magnesium ascorbyl phosphate (vitamin C), shea butter, EDTA, water

Directions

Apply to affected area not more than 3 to 4 times daily.